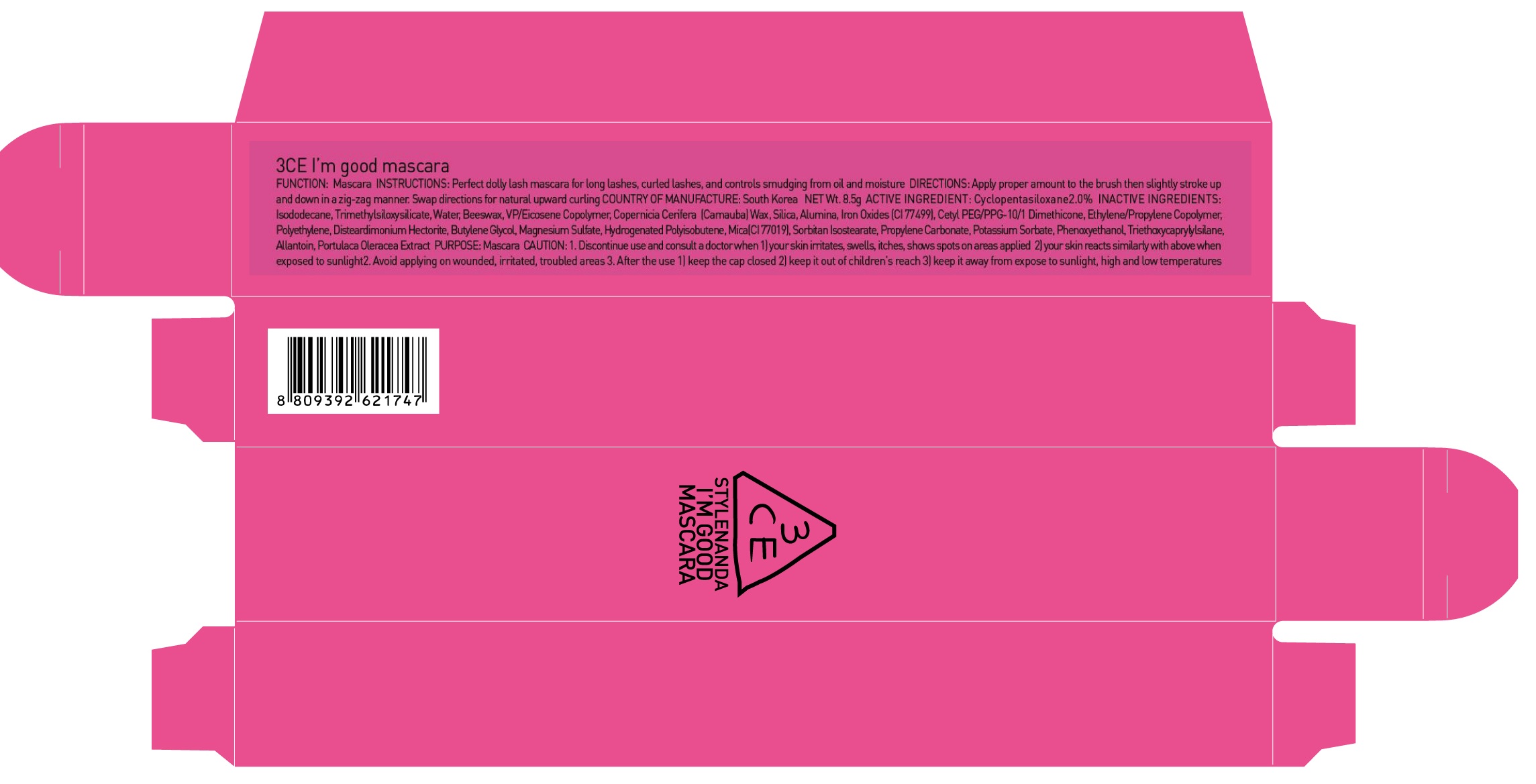 DRUG LABEL: 3CE PINK IM GOOD MASCARA
NDC: 60764-057 | Form: LIQUID
Manufacturer: Nanda Co., Ltd
Category: otc | Type: HUMAN OTC DRUG LABEL
Date: 20161004

ACTIVE INGREDIENTS: CYCLOMETHICONE 5 0.17 g/8.5 g
INACTIVE INGREDIENTS: Isododecane; Water

ACTIVE INGREDIENT

Active Ingredient: Cyclopentasiloxane 2.0%

INACTIVE INGREDIENT

Inactive Ingredients: Isododecane, Trimethylsiloxysilicate, Water, Beeswax, VP/Eicosene Copolymer, Copernicia Cerifera (Camauba) Wax, Silica, Alumina, Iron Oxides (CI 77499), Cetyl PEG/PPG-10/1 Dimethicone, Ethylene/Propylene Copolymer, Polyethylene, Disteardimonium Hectorite, Butylene Glycol, Magnesium Sulfate, Hydrogenated Polyisobutene, Mica(CI 77019), Sorbitan Isostearate, Propylene Carbonate, Potassium Sorbate, Phenoxyethanol, Triethoxycaprylylsilane, Allantoin, Portulaca Oleracea Extract

PURPOSE

Purpose: Mascara

CAUTION

CAUTION: 1. Discontinue use and consult a doctor when - your skin irritates, swells, itches, shows spots on areas applied - your skin reacts similarly with above when exposed to sunlight 2. Avoid applying on wounded, irritated, troubled areas 3. After the use - keep the cap closed - keep it out of children's reach - keep it away from expose to sunlight, high and low temperatures

KEEP OUT OF REACH OF CHILDREN

keep it out of children's reach

INSTRUCTIONS

INSTRUCTIONS: Perfect dolly lash mascara for long lashes, curled lashes, and controls smudging from oil and moisture.

Directions

Directions: Apply proper amount to the brush then slightly stroke up and down in a zig-zag manner. Swap directions for natural upward curling